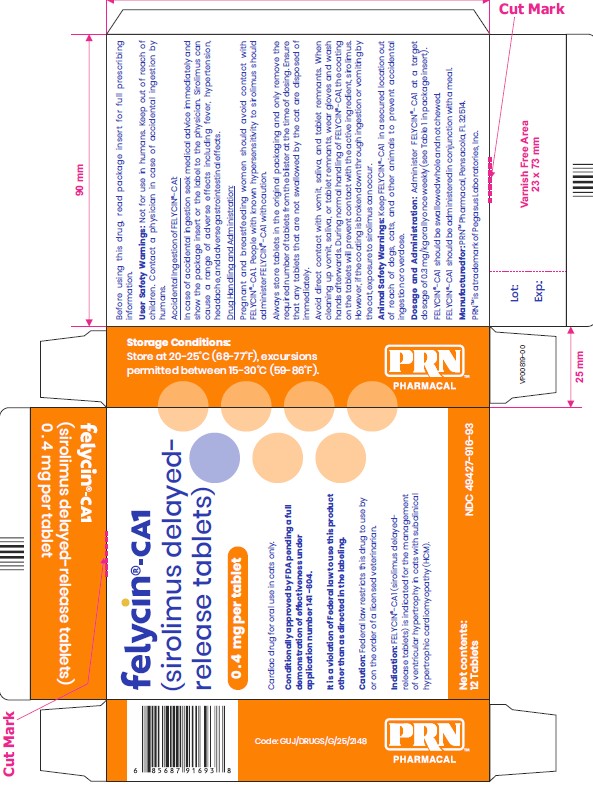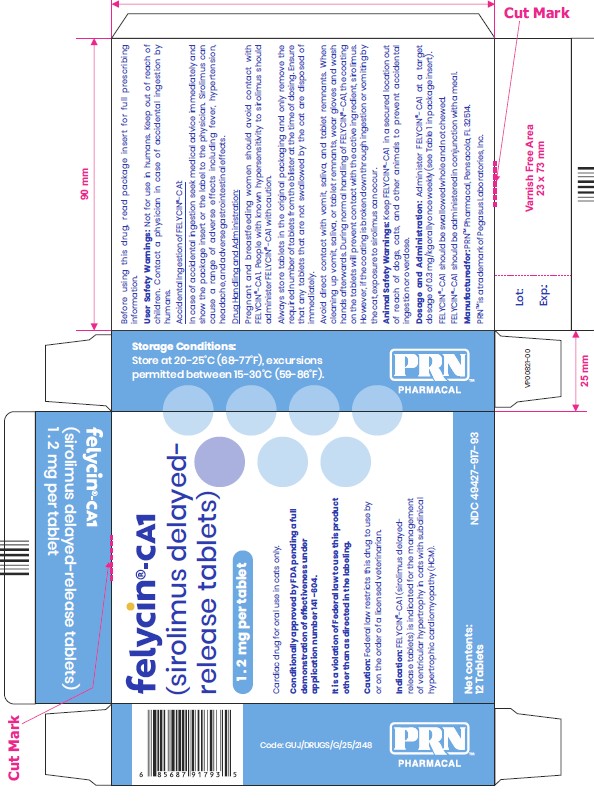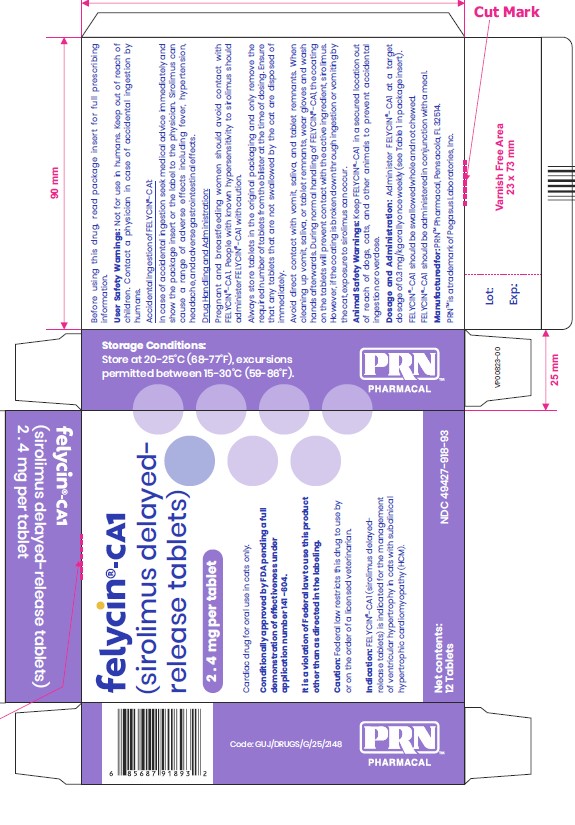 DRUG LABEL: felycin-CA1 0.4
NDC: 49427-916 | Form: TABLET
Manufacturer: Pegasus Laboratories, Inc.
Category: animal | Type: PRESCRIPTION ANIMAL DRUG LABEL
Date: 20251229

ACTIVE INGREDIENTS: SIROLIMUS 0.4 mg/1 1

felycin®-CA1 (sirolimus delayed-release tablets)

Cardiac drug for oral use in cats only

Conditionally approved by FDA pending a full demonstration of effectivenss under application number 141-604.

It is a violation of Federal law to use this product other than as directed in the labeling.

CAUTION:

Federal law restricts this drug to use by or on the order of a licensed veterinarian.

Description:

FELYCIN®-CA1 (sirolimus delayed-release tablets) contains the active ingredient sirolimus.

FELYCIN®-CA1 is available in 0.4 mg, 1.2 mg, and 2.4 mg tablet strengths.

FELYCIN®-CA1 are enteric film-coated biconvex tablets, plain on both sides. The 0.4 mg tablet is orange, the 1.2 mg tablet is blue, and the 2.4 mg tablet is white.

Indication:

FELYCIN®-CA1 (sirolimus delayed-release tablets) is indicated for the management of ventricular hypertrophy in cats with subclinical hypertrophic cardiomyopathy (HCM).

Subclinical HCM refers to cats with left ventricular (LV) hypertrophy (LV wall thickness of ≥6 mm at end diastole by 2D or M-mode assessment) in the absence of systemic hypertension, other causes of compensatory myocardial hypertrophy, current or historic symptoms of congestive heart failure, arterial thromboembolism, and severe LV outflow tract obstruction.

Dosage and Administration:

Administer FELYCIN®-CA1 at a target dosage of 0.3 mg/kg orally once weekly (see Table 1).

FELYCIN®-CA1 should be swallowed whole and not chewed. Do not split or crush tablets.

FELCYIN®-CA1 should be administered in conjunction with a meal.

Table 1: Dosing table (0.3 mg/kg once per week)
 | Number of Tablets
Body Weight (kg) | 0.4 mg | 1.2 mg | 2.4 mg
2.5 - 3.2 | 2 | 0 | 0
3.3 - 4.8 | 0 | 1 | 0
4.9 - 6.4 | 1 | 1 | 0
6.5 - 9.6 | 0 | 0 | 1
>9.6 | 0 | 1 | 1

Due to the avaiable tablet strengths, cats weighing less than 2.5 kg cannot be accurately dosed.

Contraindications:

Do not use FELYCIN®-CA1 in cats with diabetes mellitus. Discontinue immediately if a cat receiving FELYCIN®-CA1 is diagnosed with diabetes mellitus. The administration of FELYCIN®-CA1 to a cat that developed diabetes mellitus was associated with the development of diabetic ketoacidosis and death. (see Adverse Reactions).

Do not administere FELYCIN®-CA1 in cats with pre-existing liver disease (see Adverse Reactions, Precautions, and Target Animal Safety).

Warnings:

User Safety Warnings:

Not for use in humans.

Keep out of reach of children.

Contact a physician in case of accidently ingestion by humans.

Accidental Ingestion of FELYCIN®-CA1:

In case of accidental ingestion seek medical advice immediately and show the package insert or the label to the physician.

Sirolimus can cause a range of adverse effects including fever, hypertension, headache, and adverse gastrointestinal effects.

Drug Handling and Administration:

Pregnant and breastfeeding women should avoid contact with FELYCIN®-CA1.

People with known hypersenstivity to sirolimus should administer FELYCIN®-CA1 with caution.

Always store tablets in the original packaging and only remove the required number of tablets from the blister at the time of dosing.

Ensure that any tablets that are not swallowed by the cat are disposed of immediately.

Avoid direct contact with vomit, saliva, or tablet remnants. When cleaning up vomit, saliva, or tablet remnants, wear gloves and wash hands afterwards.

During normal handling of FELYCN®-CA1, the coating on the tablets will prevent contact with the active ingredient, sirolimus. However, if the coating is broken down through ingestion or vomiting by the cat, exposure to sirolimus can occur.

To obtain a copy of the Safety Data Sheet (SDS), contact PRN Pharmacal at 1-800-874-9764.

Animal Safety Warnings:

Sirolimus is a known substrate for cytochrome P-450 3A4 (CYP 3A4) and P-glycoprotein (P-gp) in humans. Administration of FELYCIN®-CA1 with drugs that inhibit CYP 3A4 or P-gp, such as calcium channel blockers, amiodarone, azoles (e.g. ketoconazole), or cyclosporine, may increase risk for toxicity. Use caution when administering FELYCIN®-CA1 in cats with the MDR1 mutation or when administering concomitantly with another P-gp substrate (e.g. eprinomectin and emodepside).

Treatment with FELYCIN®-CA1 could impact the cat's ability to mount an adequate immune response to vaccinations.

Concurrent administration of FELYCIN®-CA1 did not impact the cat's ability to mount an adequate immune reponse to a killed rabies vaccine (see Clinical Pharmacology and Target Animal Safety). The impact of concurrent administration of FELYCIN®-CA1 on vaccination for FHV-1, FCV, FPV, and FeLV has not been evaluated.

Keep FELYCIN®-CA1 in a secure location out of reach of dogs, cats and other animals to prevent accidental ingestion or overdose.

Precautions:

For use only in otherwise healthy cats with subclinical HCM in the absence of other causes of compensatory myocardial hypertrophy (e.g., systemic hypertension), current or historic symptoms of congestive heart failure, arterial thromboembolism, and severe LV outflow tract obstruction.

A diagnosis of subclinical HCM should be made by means of a comprehensive physical examination including blood pressure measurement to rule out systemic hypertension, and cardiac examination which should include echocardiography to confirm the presence of LV hypertrophy and radiography to rule out congestive heart failure.

Echocardiographic examinnation is recommended in all cases to diagnose subclinical HCM. A diagnosis of subclinical HCM is based on an end-diastolic left ventricular wall thickness of ≥6 mm measured by 2D or M-mode assessment.

Sirolimus undergoes extensive hepatic metabolism in humans. Prior to initiation of treatment with FELYCIN®-CA1, a comprehensive physical examination and screening bloodwork including a serum biochemical profile should be conducted to rule out pre-existing liver dysfunction.

Treatment with FELYCIN® -CA1 has been associated with the elevation of the transaminase enzymes, which include alanine aminotransferase (ALT) and aspartate aminotransferase (AST).

Bloodwork should be repeated 1 to 2 months following initiation of treatment, and every 6 to 12 months thereafter. If mild transaminase elevations are observed (up to 2X the upper limit of normal (ULN)), bloodwork should be repeated in
2 months. If these values remain elevated, discontinue treatment with FELYCIN®-CA1.

Discontinue treatment with FELYCIN®-CA1 if transaminase values exceed 2X the upper limit of normal, if other liver enzymes besides ALT or AST are elevated, or if clinical signs of liver dysfunction are noted.

Available information does not indicate that FELYCIN®-CA1 is immunosuppressive at the doses administered. The use of FELYCIN®-CA1 in cats with chronic viral diseases like feline viral rhinotracheitis has not been evaluated.

The safety and effectiveness of FELYCIN®-CA1 has not been evaluated in cats with other cardiomyopathy phenotypes.

The safety and effectiveness of FELYCIN®-CA1 has not been evaluated in cats receiving beta blockers or corticosteroids.

The safety and effectiveness of FELYCIN®-CA1 has not been evaluated in cats with chronic kidney disease, hyperthyroidism, or other significant systemic disease.

The effectiveness of FELYCIN®-CA1 has not been evaluated in sexually intact cats. Therefore, FELYCIN®-CA1 should not be used in animals intended for breeding.

Adverse Reactions:

In a well-controlled pilot field study, 43 cats with subclinical HCM were administered either the label dose of FELYCIN®-CA1 (0.3 mg/kg once
weekly; n=15), twice the label dose (0.6 mg/kg once weekly; n=15), or a placebo control tablet (n=13).Cats were followed for 180 days or until removal from the study (see Reasonable Expectation of Effectiveness).

Cardiac: The most frequently observed adverse reactions in cats treated with FELYCIN®-CA1 were cardiovascular in nature, relating to the
progression of HCM, and included arrhythmia, congestive heart failure, syncope, and pericardial effusion.

Three of the cats receiving twice the label dose of FELYCIN®-CA1 (0.6 mg/kg) progressed to congestive heart failure or sudden death. Two of
these cats had severe pre-existing structural disease. The third cat did not have severe structural disease at enrollment but had
markedly elevated serum N-terminal pro-brain natriuretic peptide (NTproBNP) at enrollment (1344 pmol/L, normal <100 pmol/L), which can
indicate an increased risk of disease progression. The relationship to treatment with FELYCIN®-CA1 is unknown due to the small sample size of this study and the variable disease progression of HCM.

Non-Cardiac: Other adverse reactions observed in cats treated with FELYCIN®-CA1 were lethargy, vomiting, diarrhea, and inappetence.

Diabetes Mellitus: One cat receiving the label dose (0.3 mg/kg) of FELYCIN®-CA1 developed diabetes mellitus during the study, manifesting as
hypercholesterolemia, hyperglycemia, and glucosuria with prior evidence of urinary tract infection at scheduled visits. Treatment for
diabetes was not initiated and the cat continued on the study. Subsequently, the cat presented in diabetic ketoacidosis, and despite intensive
medical management, the cat died of acute cardiac arrest.

Pre-Existing Liver Disease: In a separate pilot field study conducted in cats with chronic kidney disease (CKD), one cat was enrolled with a history
of elevated alkaline phosphatase (ALP). After treatment with the label dose (0.3 mg/kg) of FELYCIN®-CA1, this cat experienced a progressive
decline in appetite, elevation of liver enzymes, including ALP, ALT, and AST, and icterus, and was euthanized approximately 4 months after exiting the study.

Contact Information:

To report suspected adverse drug experiences or for technical assistance contact PRN Pharmacal at 1-800-874-9764.

For additional information about reporting adverse drug experiences for animal drugs, contact FDA at 1-888-FDA-VETS or online at www.fda.gov/reportanimalae.

Clinical Pharmacology:

Mode of Action:
Sirolimus is an immunosuppressant that targets and inhibits the mammalian target of rapamycin C1 (mTORC1) protein complex, a central regulator of cell growth and nutrient response. Studies in rodent models suggest mTOR inhibition by sirolimus attenuates cardiac hypertrophy by promoting autophagy, attenuating oxidative stress and blocking pro-inflammatory responses, thereby resulting in an improvement in cardiac function in rodents.

Pharmacokinetics:
In a laboratory safety study in healthy adult cats after repeat oral dosing of FELYCIN®-CA1 once per week for 24 weeks (See Target Animal Safety), mean dose normalized maximum plasma concentration (Cmax) values decreased with an increasing dose suggesting that absorption of sirolimus may be saturated at higher dosing levels in cats. The comparison between the area under the curve from dosing extrapolated to infinity (AUCinf) at Day 0 and area under the curve from the time of dosing to the last quantifiable concentration (AUClast) at Day 147 suggests the pharmacokinetics are non-linear after multiple dosing.

At 0.38 mg/kg, accumulation was observed between Days 0 and 147 with geometric mean accumulation ratios for the Cmax and area under the curve AUClast of 1.33 and 1.62, respectively.

Table 2 Arithmetic mean (±standard deviation) of sirolimus pharmacokinetic parameters following the first administration of FELYCIN®-CA1 (maximum proposed label dose 0.38 mg per kg body weight) in male and female cats in a laboratory study.
Parameter | Estimate
AUClast(h*ng/mL) | 288 ± 198
Cmax(ng/mL) | 22.0 ± 15.8
t1/2(h) | 71.8 ± 42.0
Tmax(h)* | 1.50 (1.00-12.0)

AUClast = area under the curve from dosing to 168 hours
Cmax = maximum plasma concentration

t1/2 = half-life
Tmax= time to maximum plasma concentration

*Median (range)

Reasonable Expectation of Effectiveness:

A reasonable expectation of effectiveness may be demonstrated based on evidence such as, but not limited to, pilot data in the target species or studies from published literature.
FELYCIN®-CA1 is conditionally approved pending a full demonstration of effectiveness.

Additional information for Conditional Approvals can be found at www.fda.gov/animalca.

A reasonable expectation of effectiveness for FELYCIN®-CA1 is based on published scientific literature and results from a pilot field study conducted at two US referral cardiology centers.

Published literature, including studies in a mouse model of concentric left ventricular (LV) hypertrophy and in human patients following cardiac transplantation, demonstrated that sirolimus decreased LV hypertrophy and improved diastolic function.

Pilot Field Study:
A well-controlled pilot field study enrolled a total of 43 cats of various breeds. The cats received either FELYCIN®-CA1 at the label dose of 0.3 mg/kg once weekly (n=15), FELYCIN®-CA1 at 0.6 mg/kg once weekly (n=15), or placebo control tablets once weekly (n=13).

Cats ranged between 1 and 12 years of age and weighed between 3.3 and 14 kg at enrollment; 37 of the 43 cats were male. Cats were confirmed to have evidence of subclinical HCM prior to enrollment based on echocardiographic findings of LV hypertrophy (LV wall thickness of ≥6 mm at end diastole by 2D or M-mode assessment), with no evidence of congestive heart failure (CHF), arterial thromboembolism, or arrhythmias requiring specific anti-arrhythmic therapy. Cats were ineligible if they were found to have evidence of cardiogenic pulmonary edema, severe LV outflow tract obstruction (LV outflow tract gradient ≤50 mmHg), clinically significant tachyarrhythmias, cardiac disease other than HCM, systemic hypertension, significant systemic di sease, or were recei vi ng l ong- term corticosteroid treatment. Concomitant use of oral clopidogrel and/or angiotensin-converting enzyme (ACE) inhibitors was permitted if administered for at least 2 weeks prior to study enrollment. No new cardiac medications were permitted during the study.

Exploratory analyses were conducted evaluating measures of LV hypertrophy and left atrial dilation in addition to comparing the relationship between disease progression/response and baseline patient characteristics. Effectiveness was based on changes in maximum wall thickness (MWT) of the LV.

Of the 43 cats enrolled in the study, 36 cats were still enrolled at the final evaluation on Day 180. Six cats (5 high dose and 1 control) were excluded due to the progression of heart disease, death, or owner removal.

Echocardiographic values were comparable between the three study groups at baseline. Following 180 days of treatment, differences in LV MWT were evident. Cats treated with 0.3 mg/kg (label dose) of FELYCIN®-CA1 had a lower mean MWT and the difference between the 0.3 mg/kg FELYCIN®-CA1 group and the control group was statistically significant across Day 60 and Day 180. No statistically significant treatment effects were detected for other echocardiographic values.

Within the 36 evaluable cases at Day 180, MWT decreased by a mean value of 0.17 mm in the 0.3 mg/kg (label dose) group (n=14). In contrast, MWT increased by a mean of 0.94 mm in the placebo group (n=12), and by 0.50 mm in the 0.6 mg/kg group (n=10).

Target Animal Safety:

Margin of Safety Study:
A 24-week laboratory margin of safety study was conducted in 32 healthy laboratory cats, aged 10 to 11 months at enrollment. Cats were randomized into 4 groups of 8 cats with 4 male and 4 female cats in each group. FELYCIN®-CA1 was administered at a dose of 0, 0.38, 1.13, and
1.88 mg/kg (0X, 1.3X, 3.8X, and 6.3X the label dose of 0.3 mg/kg) for 24 weeks. Cats were dosed in a fed state and cats in the control group were untreated. No clinically significant effects on physical examination, food consumption, bodyweight, or postmortem examination parameters were identified.

Of the 24 cats that received FELYCIN®-CA1, 15 cats experienced at least one transaminase value elevation (i.e., AST and ALT) during the course of the study. These cats were in all 3 FELYCIN®-CA1 dosing groups and a dose-response was not present. Transaminase elevations were not observed in the control cats. Some of the elevations were transient and/or mild (i.e., less than 2X the upper limit of the reference range). Four male littermates were found to have the most severe elevations, with maximum AST values of 110 to 515 U/L (reference range 16 to 34 U/L) and maximum ALT values of 255 to 4552 U/L (reference range 41 to 160 U/L). Transaminase elevations were recorded at the first bloodwork collection time point (Day 26/27) after the treatment initiation in 3 of the 4 littermates, and elevations were present throughout the 24-week dosing period. All affected cats remained clinically normal and postmortem examination revealed no signs of liver pathology.

Pilot Safety Study:
In a pilot laboratory study, 32 cats (11 males and 21 females, aged 2 to 5 years) were allocated to 4 groups of 8 cats. FELYCIN®-CA1 was administered 3 times per week at doses of 0, 0.15, 0.45, or 0.75 mg/kg (0X, 1.5X, 4.5X, or 7.5X the label dose) for 4 weeks, followed by a 4-week recovery period. The clinical observations, physical examinations, and body weight evaluations did not reveal findings of clinical or toxicological significance during the study. Mild transaminase elevations were observed in 8 of the 24 cats receiving FELYCIN®-CA1. By Day 55, all ALT values were within the reference range and AST values were either within the reference range or showing a downward trend after the discontinuation of treatment with FELYCIN®-CA1.

Vaccine Response Study:
In a laboratory study, 20 healthy, vaccine-naïve cats (4 per sex in the control group and 6 per sex in the treated group), approximately 4 months of age at study initiation were administered FELYCIN®-CA1 at 0 and 0.9 mg/kg (0X and 3X the label dose) once a week for 56 days (Days 0, 7, 14, 21, 28, 35, 42, 49, and 56). Cats were dosed in a fed state and the control cats were sham dosed. A commercially available killed rabies vaccine was administered to all cats on Day 29. All cats (control and treated) in the study demonstrated an adequate immune (serologic) response to the killed rabies virus vaccine on Day 57. The clinical observations, physical examinations, and clinical pathology assessments revealed no clinically significant abnormal findings.

How supplied:

FELYCIN®-CA1 (sirolimus delayed-release tablets) 0.4 mg, 1.2 mg and 2.4 mg are enteric film-coated biconvex tablets, plain on both sides.
FELYCIN®-CA1 is supplied in a carton containing a child resistant blister with 12 tablets.

Storage Conditions:

Store at 20-25˚C (68-77˚F), excursions permitted between 15-30˚C (59-86˚F).

Manufactured For:

PRN™ Pharmacal, Pensacola, FL 32514.

PRN™ is a trademark of Pegasus Laboratories, Inc.

VP00824-01

Revision Date: May-2025